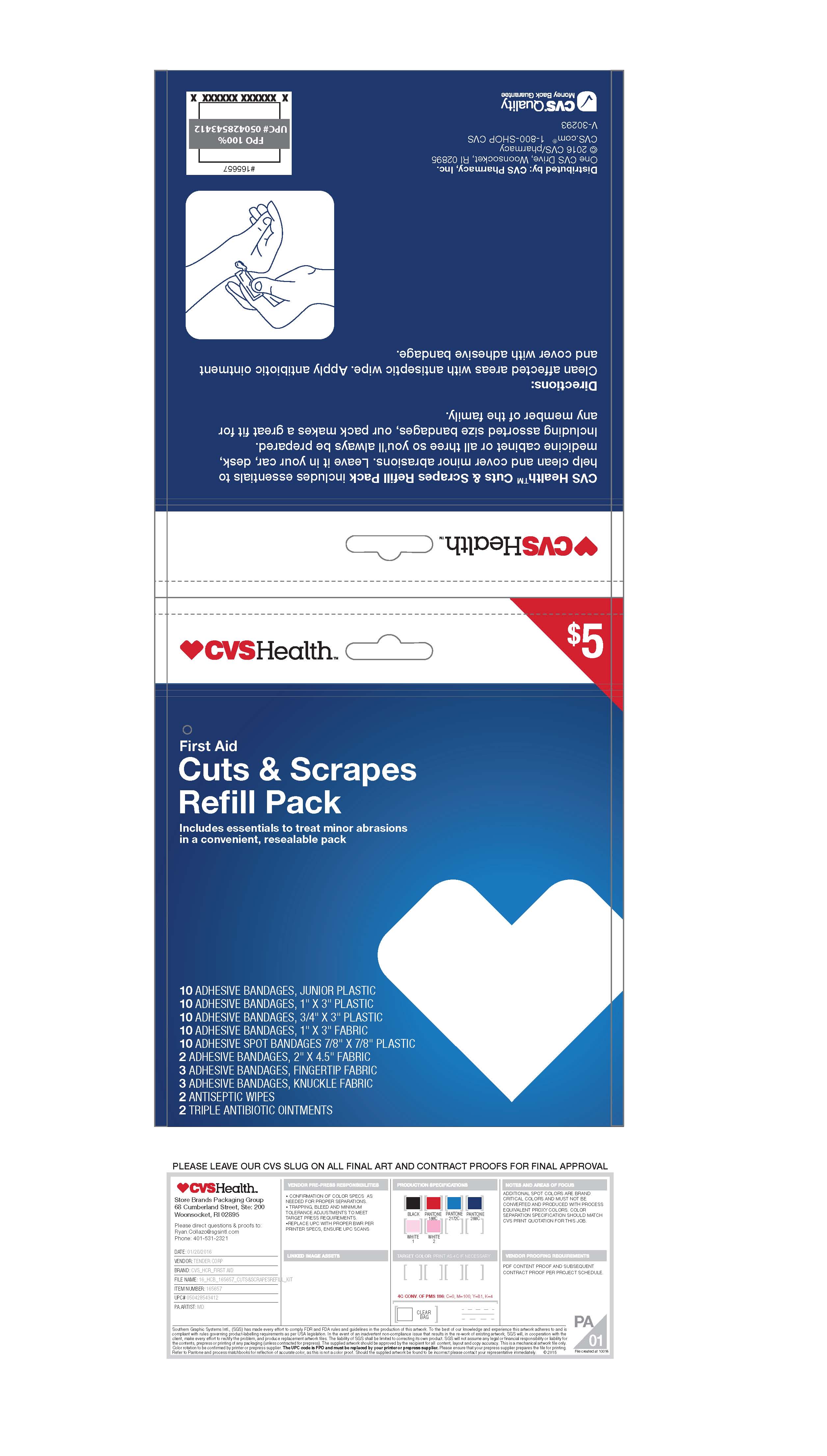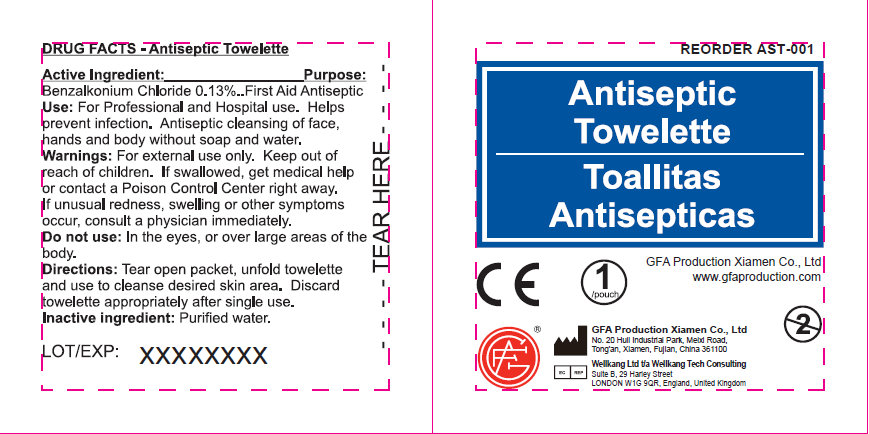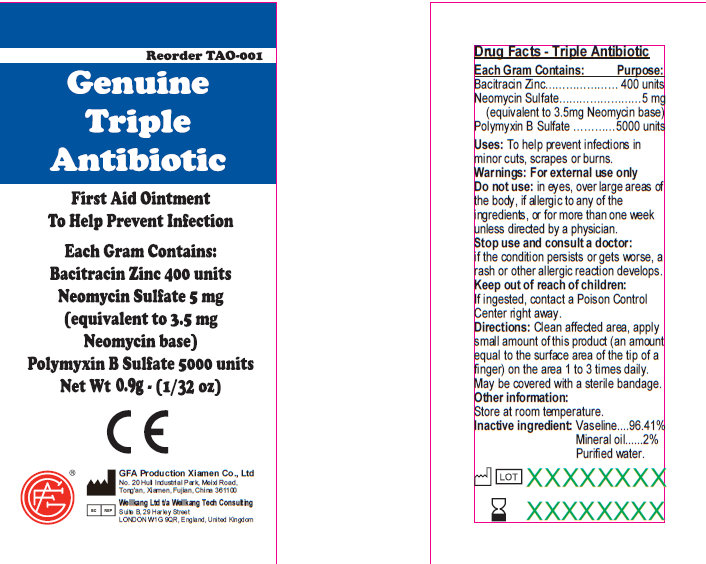 DRUG LABEL: CVS Cuts and Scrapes Refill Pack
NDC: 69842-402 | Form: KIT | Route: TOPICAL
Manufacturer: CVS
Category: otc | Type: HUMAN OTC DRUG LABEL
Date: 20161227

ACTIVE INGREDIENTS: BENZALKONIUM CHLORIDE 1.3 mg/1 mL; BACITRACIN ZINC 400 [iU]/1 g; NEOMYCIN SULFATE 5 mg/1 g; POLYMYXIN B SULFATE 5000 [iU]/1 g
INACTIVE INGREDIENTS: WATER; PETROLATUM; MINERAL OIL; WATER

CVS Cuts & Scrapes Refill Pack

Active Ingredient

Benzalkonium Chloride .13%

Purpose

First Aid Antiseptic

Use

For Professional and Hospital use. Helps prevent infection. Antiseptic cleansing of face, hands and body without soap and water.

Warnings

For external use only. Keep out of reach of children. If swallowed, get medical help or contact a Poison Control Center right away. If unusual redness, swelling or other symptoms occur, cunsult a physician immediately.

Do not use

In the eyes, or over large areas of the body

Directions

Tear open packet, unfold towelette and use to cleanse desired skin are. Discard towelette appropriately after single use

Inactive Ingredients

Purified Water

Active Indredients

Bacitracin Zinc 400 units

Neomycin Sulfate 5mg (equivalent to 3.5 mg Neomycin base)

Polymyxin B Sulfate 5000 units

Purpose

Triple Antibiotic

Uses

To help prevent infection in:
minor cuts; scrapes; burns

Warnings

For external use only

Keep out of reach of children.

If ingested, contact a Poison

Control Center right away.

Stop use and consult a doctor:

if the condition persists or gets worse; a rash or other allergic reaction develops

Do not use: in eyes; over large areas of the body;

If allergic to any of the ingredients; for more than one week unless directed by a physician.

Directions

Directions: clean affected area; apply small amount of this product (an amount equal to the surface area of the tip of a finger) on the area 1 to 3 times daily; may be covered with a sterile bandage

Storage and Handling

Other information:

Store at room temperature.

INACTIVE INGREDIENT

Vaseline
Mineral Oil
Purified Water

Antiseptic Towelette

GFA Production Xiamen Co., Ltd
www.gfaproduction.com

PACKAGE LABEL

Genuine Triple Antibiotic

First Aid Ointment

To Help Prevent Infection

Each Gram Contains:

Bacitracin Zinc 400 units

Neomycin Sulfate 5 mg

(equivalent to 3.5 mg

Neomycin base)

Polymyxin B Sulfate 5000 units

Net Wt. 0.5g ; (1/64 oz)

Manufactured in CHINA for

GENUINE FIRST AID.

Triple Antibiotic Ointment 10pcs

Net wt. 0.9g (1/32oz)

100
Triple Antibiotic